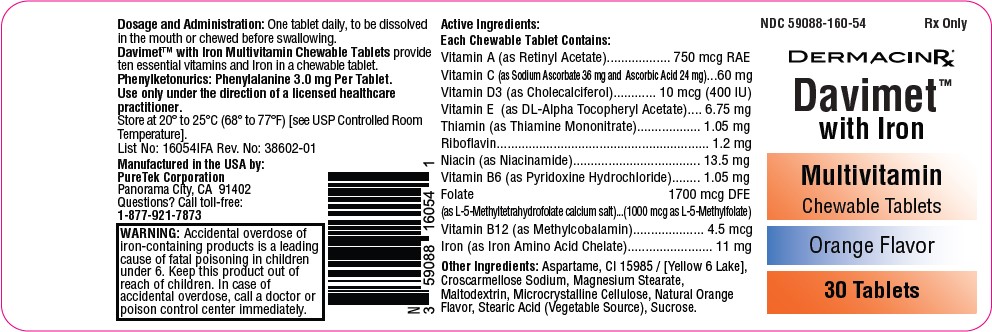 DRUG LABEL: Davimet with Iron
NDC: 59088-160 | Form: TABLET
Manufacturer: PureTek Corporation
Category: prescription | Type: HUMAN PRESCRIPTION DRUG LABEL
Date: 20241127

ACTIVE INGREDIENTS: VITAMIN A ACETATE 750 ug/1 1; ASCORBIC ACID 24 mg/1 1; NIACINAMIDE 13.5 mg/1 1; PYRIDOXINE HYDROCHLORIDE 1.05 mg/1 1; THIAMINE MONONITRATE 1.05 mg/1 1; CHOLECALCIFEROL 10 ug/1 1; IRON 11 mg/1 1; RIBOFLAVIN 1.2 mg/1 1; METHYLCOBALAMIN 4.5 ug/1 1; SODIUM ASCORBATE 36 mg/1 1; LEVOMEFOLATE CALCIUM 1000 ug/1 1; .ALPHA.-TOCOPHEROL ACETATE, DL- 6.75 mg/1 1
INACTIVE INGREDIENTS: MICROCRYSTALLINE CELLULOSE; SUCROSE; MALTODEXTRIN; MAGNESIUM STEARATE; ASPARTAME; STEARIC ACID; FD&C YELLOW NO. 6; CROSCARMELLOSE SODIUM

Davimet with Iron

DESCRIPTION:

Each caplet contains:
Vitamin A (as Retinyl Acetate).......................................750 mcg RAE
Vitamin C (as Sodium Ascorbate 36 mg and Ascorbic Acid 24 mg)........ 60 mg
Vitamin D3 (as Cholecalciferol)................................. 10 mcg (400 IU)
Vitamin E (as DL-Alpha Tocopheryl Acetate)........................ 6.75 mg
Thiamin (as Thiamine Mononitrate)....................................... 1.05 mg
Riboflavin................................................................................. 1.2 mg
Niacin (as Niacinamide).......................................................... 13.5 mg
Vitamin B6 (as Pyridoxine Hydrochloride)............................. 1.05 mg
Folate (as L-5-Methyltetrahydrofolate calcium salt)…1700 mcg DFE
(1000 mcg as L-5-Methylfolate)
Vitamin B12 (as Methylcobalamin)......................................... 4.5 mcg
Iron (as Iron Amino Acid Chelate)............................................... 11 mg

Other Ingredients: Aspartame, CI 15985 / [Yellow 6 Lake], Croscarmellose Sodium, Magnesium Stearate, Maltodextrin, Microcrystalline Cellulose, Natural OrangeFlavor, Stearic Acid (Vegetable Source), Sucrose.

Phenylketonurics: Phenylalanine 3.0 mg Per Tablet.

INDICATIONS AND USAGE:

Davimet™ with Iron Multivitamin Chewable Tablets are indicated for the treatment of iron deficiency anemia and folate deficiency, commonly seen in conditionssuch as extended convalescence, menorrhagia, pregnancy, puberty, excessive blood loss, and advanced age. They are also indicated for condition in which irondeficiency and vitamin C deficiency occur together, along with a deficient intake or increased need for B-Complex vitamins in chronic and acute illness, as well as casesof metabolic stress, and in convalescence.

CONTRAINDICATIONS:

This product is contraindicated in patients with known hypersensitivity to any of its ingredients; also, all iron compounds are contraindicated in patients withhemosiderosis, hemochromatosis, or hemolytic anemias. Pernicious anemia is a contraindication, as folic acid may obscure its signs and symptoms.

WARNING:

Keep out of the reach of children. In case of accidental overdose, seek professional assistance or contact a Poison Control Center immediately.

Accidental overdose of iron-containing products is a leading cause of fatal poisoning in children under 6. Keep this product out of reach of children. In case of accidentaloverdose, call a doctor or poison control center immediately.

Administration of folate alone is improper therapy for pernicious anemia and other megaloblastic anemias in which vitamin B12 is deficient.
CAUTION: Should be chewed.

PRECAUTIONS:

Folate in doses above 0.1 mg daily may obscure pernicious anemia, in that hematologic remission can occur while neurological manifestations remain progressive.There is a potential danger in administering folate to patients with undiagnosed anemia, since folate may obscure the diagnosis of pernicious anemia by alleviatingthe hematologic manifestations of the disease while allowing the neurologic complications to progress. This may result in severe nervous system damage before thecorrect diagnosis is made. Adequate doses of vitamin B12 may prevent, halt, or improve the neurologic changes caused by pernicious anemia.

The patient’s medical conditions and consumption of other drugs, herbs, and/or supplements should be considered.

Use only under the direction of a licensed healthcare practitioner. Call your doctor about side effects. To report side effects, call PureTek Corporation at 1-877-921-7873 or FDA at 1-800-FDA-1088 or www.fda.gov/medwatch.

Drug Interactions:

Davimet™ with Iron Multivitamin Chewable Tablets are not recommended and should not be given to patients receiving levodopa because the action oflevodopa is antagonized by pyridoxine. There is a possibility of increased bleeding due to pyridoxine interaction with anticoagulants (e.g., Aspirin, Heparin orClopidogrel).

Adverse Reactions:

Folate: Allergic sensitizations have been reported following both oral and parenteral administration of folate.

Iron: Gastrointestinal disturbances (anorexia, nausea, diarrhea, constipation) occur occasionally, but are usually mild and may subside with continuation of therapy.Although the absorption of iron is best when taken between meals, giving Davimet™ with Iron Multivitamin Chewable Tablets after meals may controloccasional gastrointestinal disturbances. Davimet™ with Iron Multivitamin Chewable Tablets is best absorbed when taken at bedtime.

Adverse reactions have been reported with specific vitamins and minerals but generally at levels substantially higher than those contained herein. However, allergicand idiosyncratic reactions are possible at lower levels. Iron, even at the usual recommended levels, has been associated with gastrointestinal intolerance in somepatients

OVERDOSE:

Iron: Signs and Symptoms: Iron is toxic. Acute overdosage of iron may cause nausea and vomiting and, in severe cases, cardiovascular collapse and death. Othersymptoms include pallor and cyanosis, melena, shock, drowsiness and coma. The estimated overdose of orally ingested iron is 300 mg/kg body weight. Whenoverdoses are ingested by children, severe reactions, including fatalities, have resulted. Davimet™ with Iron Multivitamin Chewable Tablets should be stored beyond the reach of children to prevent against accidental iron poisoning.

Treatment:

For specific therapy, exchange transfusion and chelating agents should be used. For general management, perform gastric lavage with sodium bicarbonate solutionor milk. Administer intravenous fluids and electrolytes and use oxygen.

DOSAGE AND ADMINISTRATION:

One tablet daily, to be dissolved in the mouth or chewed before swallowing.

Do not use if bottle seal is broken.
KEEP THIS AND ALL MEDICATIONS OUT OF THE REACH OF CHILDREN.
Store at 20° to 25°C (68° to 77°F) [see USP Controlled Room Temperature].

HOW SUPPLIED:

Davimet™ with Iron Multivitamin Chewable Tablets are light orange with speckles, orange flavor, un-scored, round tablets. Available on prescription only in bottleof 30 tablets – NDC 59088-160-54. Dispense in a tight, light resistant container with a child resistant closure as defined in the USP/NF. All prescription substitutionsusing this product shall be pursuant to state statutes as applicable. This is not an Orange Book product.

Davimet™ with Iron

Manufactured by:
PureTek Corporation
Panorama City, CA 91402
For questions or information
call toll-free: 877-921-7873